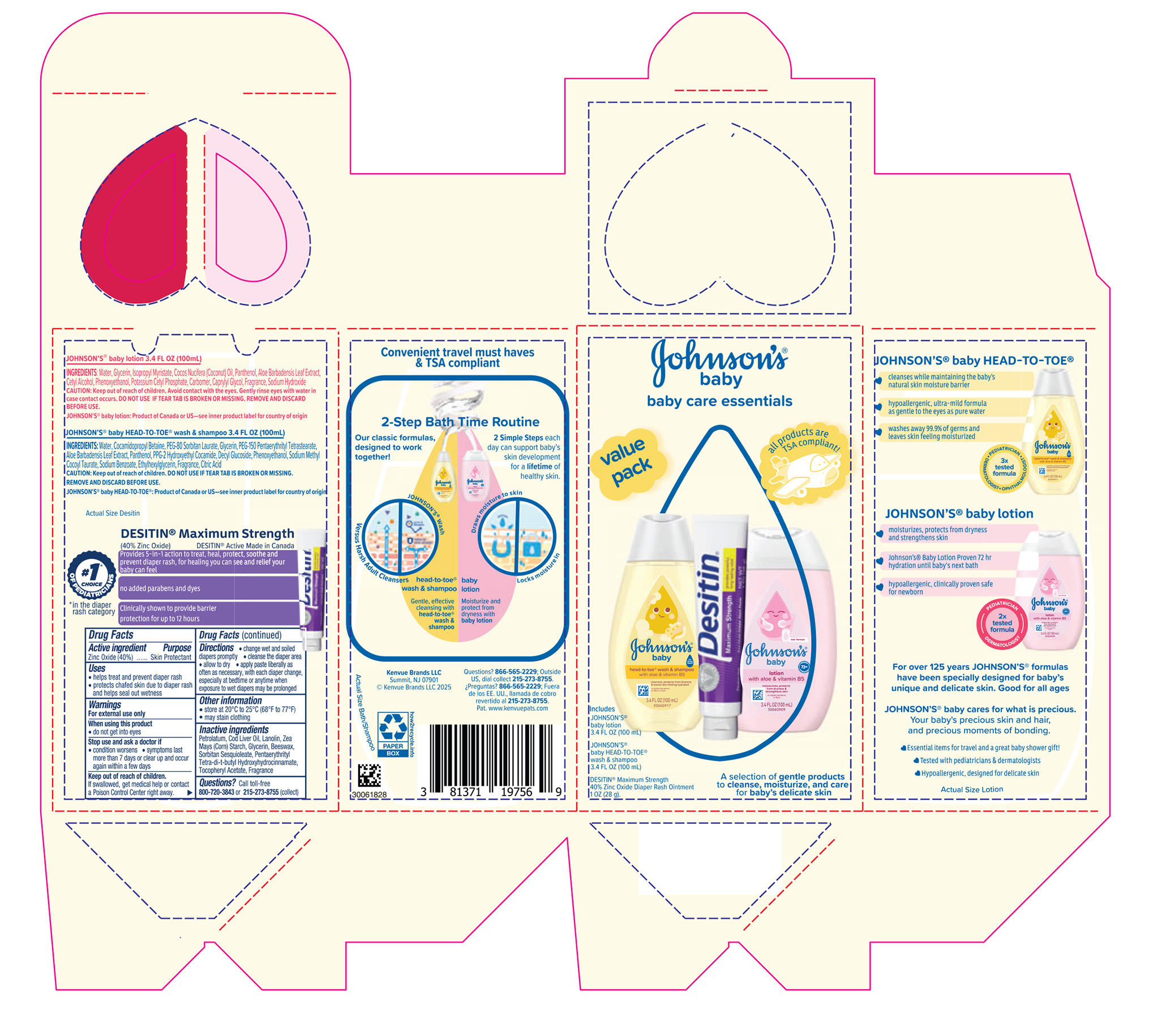 DRUG LABEL: Johnsons Baby Care Essentials Gift Set		
NDC: 69968-0953 | Form: KIT | Route: TOPICAL
Manufacturer: Kenvue Brands LLC
Category: otc | Type: HUMAN OTC DRUG LABEL
Date: 20251124

ACTIVE INGREDIENTS: ZINC OXIDE 400 mg/1 g
INACTIVE INGREDIENTS: PENTAERYTHRITOL TETRAKIS(3-(3,5-DI-TERT-BUTYL-4-HYDROXYPHENYL)PROPIONATE); PETROLATUM; COD LIVER OIL; LANOLIN; ZEA MAYS (CORN) STARCH; GLYCERIN; SORBITAN SESQUIOLEATE; BEESWAX; ALPHA-TOCOPHEROL ACETATE

Johnsons Baby Care Essentials Gift Set

DESITIN Maximum Strength Zinc Oxide Diaper Rash

Drug Facts

Active ingredient

Zinc Oxide (40%)

Purpose

Skin Protectant

Uses

• helps treat and prevent diaper rash

• protects chafed skin due to diaper rash and helps seal out wetness

Warnings

For external use only

When using this product

• do not get into eyes

Stop use and ask a doctor if

• condition worsens

• symptoms last more than 7 days or clear up and occur again within a few days

Keep out of reach of children.

If swallowed, get medical help or contact a Poison Control Center right away.

Directions

• change wet and soiled diapers promptly

• cleanse the diaper area

• allow to dry

• apply paste liberally as often as necessary, with each diaper change, especially at bedtime or anytime when exposure to wet diapers may be prolonged

Other information

• store at 20°C to 25°C (68°F to 77°F)

• may stain clothing

Inactive ingredients

Petrolatum, Cod Liver Oil, Lanolin, Zea Mays (Corn) Starch, Glycerin, Beeswax, Sorbitan Sesquioleate, Pentaerythrityl Tetra-di-t-butyl Hydroxyhydrocinnamate, Tocopheryl Acetate, Fragrance

Questions?

Call toll-free 800-720-3843 or 215-273-8755 (collect)

Distributed by:
Kenvue brands LLC

Summit, NJ 07901

PRINCIPAL DISPLAY PANEL - Kit Package

Johnson’s®

baby

baby care essentials

value

pack

all products are

TSA compliant!

Includes

JOHNSON’S® baby lotion 3.4 FL OZ (100 mL)

JOHNSON’S® baby HEAD-TO-TOE® wash & shampoo 3.4 FL OZ (100 mL)

DESITIN® Maximum Strength 40% Zinc Oxide Diaper Rash Ointment 1 OZ (28 g).

A selection of gentle products to cleanse, moisturize, and care for baby’s delicate skin